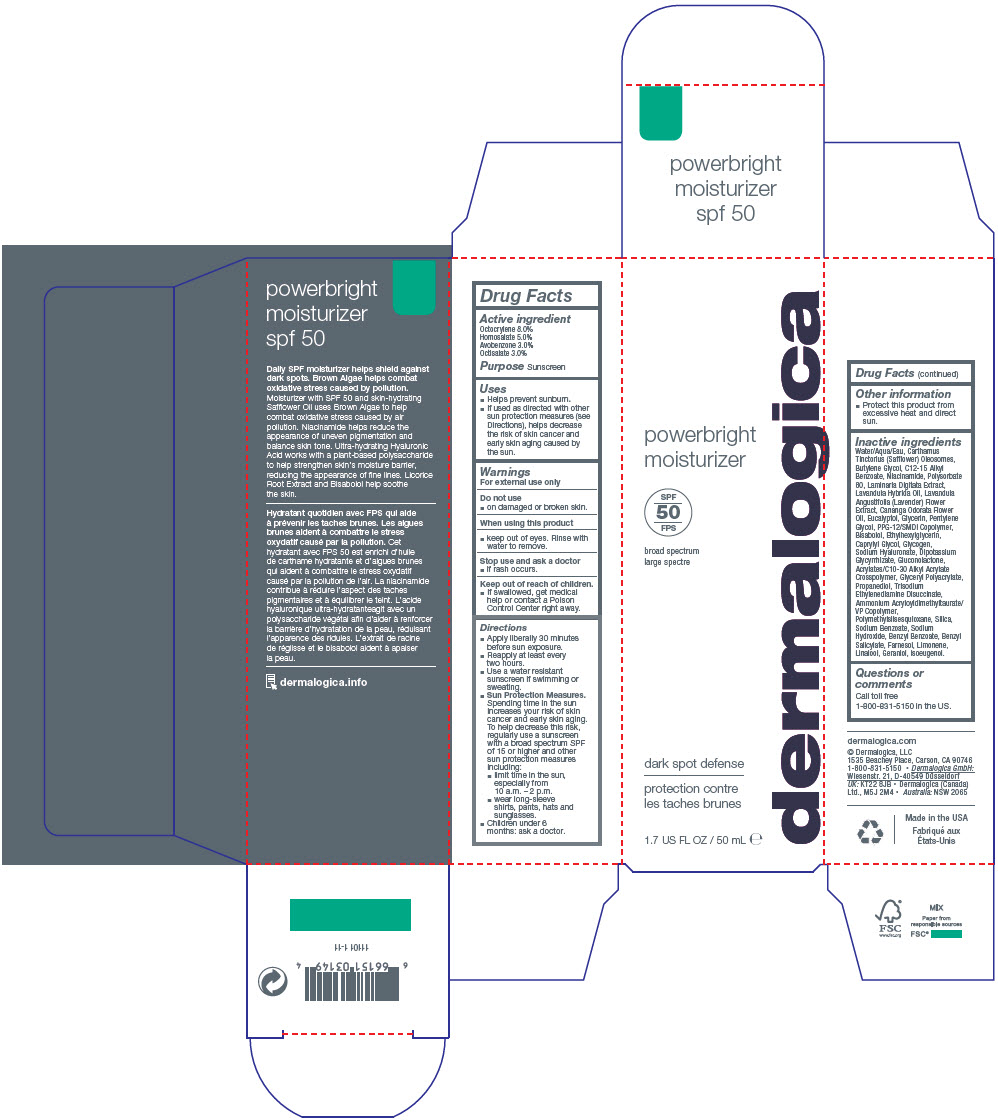 DRUG LABEL: Powerbright Moisturizer SPF 50
NDC: 68479-020 | Form: LOTION
Manufacturer: Dermalogica, LLC.
Category: otc | Type: HUMAN OTC DRUG LABEL
Date: 20241227

ACTIVE INGREDIENTS: Octocrylene 80 mg/1 mL; Homosalate 50 mg/1 mL; Avobenzone 30 mg/1 mL; Octisalate 30 mg/1 mL
INACTIVE INGREDIENTS: Water; SAFFLOWER OIL; Butylene Glycol; ALKYL (C12-15) BENZOATE; Niacinamide; Polysorbate 80; Glycerin; Ammonium Acryloyldimethyltaurate/VP Copolymer; Pentylene Glycol; Propanediol; POLYMETHYLSILSESQUIOXANE (4.5 MICRONS); PPG-12/Smdi Copolymer; Caprylyl Glycol; Glycogen; LAVANDIN OIL; YLANG-YLANG LEAF OIL; SILICON DIOXIDE; LEVOMENOL; Gluconolactone; Ethylhexylglycerin; HYALURONATE SODIUM; GLYCYRRHIZINATE DIPOTASSIUM; Trisodium Ethylenediamine Disuccinate; Sodium Benzoate; Sodium Hydroxide; LAMINARIA DIGITATA; Eucalyptol; LAVANDULA ANGUSTIFOLIA SUBSP. ANGUSTIFOLIA FLOWER; LINALOOL, (+/-)-; Benzyl Benzoate; Benzyl Salicylate; Farnesol; LIMONENE, (+)-; Geraniol; Isoeugenol

Powerbright Moisturizer SPF 50

Drug Facts

Active ingredient

Octocrylene 8.0%
Homosalate 5.0%
Avobenzone 3.0%
Octisalate 3.0%

Purpose

Sunscreen

Uses

- Helps prevent sunburn.
- If used as directed with other sun protection measures (see Directions), helps decrease the risk of skin cancer and early skin aging caused by the sun.

Warnings

For external use only

Do not use

- on damaged or broken skin.

When using this product

- keep out of eyes. Rinse with water to remove.

Stop use and ask a doctor

- if rash occurs.

Keep out of reach of children.

- If swallowed, get medical help or contact a Poison Control Center right away.

Directions

- Apply liberally 30 minutes before sun exposure.
- Reapply at least every two hours.
- Use a water resistant sunscreen if swimming or sweating.
- Sun Protection Measures. Spending time in the sun increases your risk of skin cancer and early skin aging. To help decrease this risk, regularly use a sunscreen with a broad spectrum SPF of 15 or higher and other sun protection measures including:
  - limit time in the sun, especially from 10 a.m. – 2 p.m.
  - wear long-sleeve shirts, pants, hats and sunglasses.
- Children under 6 months: ask a doctor.

Other information

- Protect this product from excessive heat and direct sun.

Inactive ingredients

Water/Aqua/Eau, Carthamus Tinctorius (Safflower) Oleosomes, Butylene Glycol, C12-15 Alkyl Benzoate, Niacinamide, Polysorbate 80, Laminaria Digitata Extract, Lavandula Hybrida Oil, Lavandula Angustifolia (Lavender) Flower Extract, Cananga Odorata Flower Oil, Eucalyptol, Glycerin, Pentylene Glycol, PPG-12/SMDI Copolymer, Bisabolol, Ethylhexylglycerin, Caprylyl Glycol, Glycogen, Sodium Hyaluronate, Dipotassium Glycyrrhizate, Gluconolactone, Acrylates/C10-30 Alkyl Acrylate Crosspolymer, Glyceryl Polyacrylate, Propanediol, Trisodium Ethylenediamine Disuccinate, Ammonium Acryloyldimethyltaurate/ VP Copolymer, Polymethylsilsesquioxane, Silica, Sodium Benzoate, Sodium Hydroxide, Benzyl Benzoate, Benzyl Salicylate, Farnesol, Limonene, Linalool, Geraniol, Isoeugenol.

Questions or comments

Call toll free
1-800-831-5150 in the US.

PRINCIPAL DISPLAY PANEL - 50 mL Bottle Carton

powerbright
moisturizer

SPF
50

broad spectrum

dark spot defense

1.7 US FL OZ / 50 mL e

dermalogica